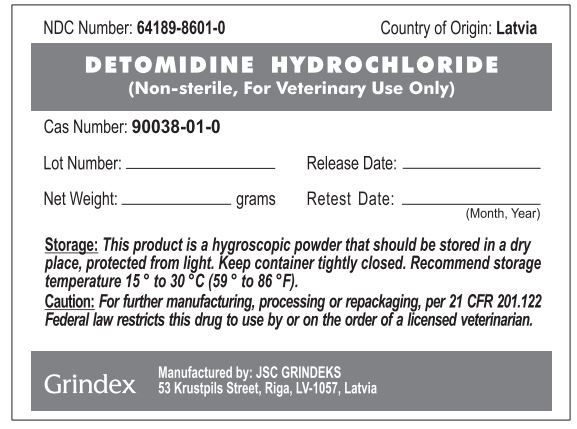 DRUG LABEL: Detomidine Hydrochloride
NDC: 64189-8601 | Form: POWDER
Manufacturer: GRINDEKS Joint Stock Company
Category: other | Type: BULK INGREDIENT - ANIMAL DRUG
Date: 20251216

ACTIVE INGREDIENTS: DETOMIDINE HYDROCHLORIDE 1 g/1 g

Detomidine Hydrochloride

WARNINGS AND PRECAUTIONS

Caution: For further manufacturing, processing, or repackaging, per 21 CFR 201.122

Federal Law restricts this drug to use by or on the order of a licensed veterinarian.

STORAGE AND HANDLING

Storage: This product is a hygroscopic powder that should be stored in a dry place, protected from light. Keep container tightly closed. Recommend storage temperature 15° to 30°C (59° to 86°F).

PACKAGE LABEL

NDC Number: 64189-8601-0 Country of Origin: Latvia

DETOMIDINE HYDROCHLORIDE

(Non-sterile, For Veterinary Use Only)

Cas Number: 90038-01-0

Lot Number:_______________ Release Date:____________

Net Weight:____________grams Retest Date:_____________ (Month, Year)

Storage: This product is a hygroscopic powder that should be stored in a dry place, protected from light. Keep container tightly closed. Recommend storage temperature 15° to 30°C (59° to 86°F).

Caution: For further manufacturing, processing, or repackaging, per 21 CFR 201.122. Federal law restricts this drug to use by or on the order of a licensed veterinarian.

Grindex

Manufactured by: JSC GRINDEKS

53 Krustpils Street, Riga, LV-1057, Latvia